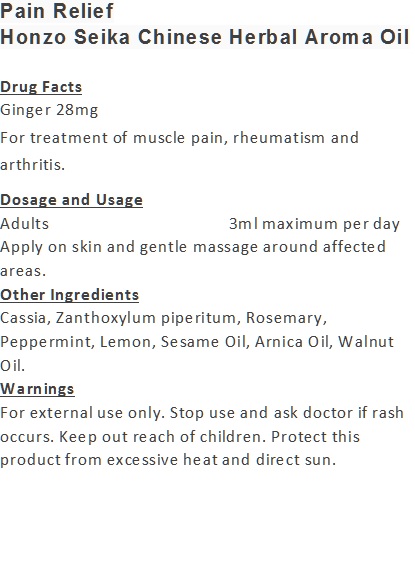 DRUG LABEL: Pain Relief
NDC: 71263-9915 | Form: OIL
Manufacturer: NIC CO., LTD.
Category: otc | Type: HUMAN OTC DRUG LABEL
Date: 20170101

ACTIVE INGREDIENTS: GINGER 28 mg/100 mL
INACTIVE INGREDIENTS: SESAME OIL; CINNAMOMUM CASSIA WHOLE; WALNUT OIL; ARNICA MONTANA ROOT; ZANTHOXYLUM PIPERITUM WHOLE; ROSEMARY OIL; PEPPERMINT OIL; LEMON OIL

Drug Facts

Ginger 28mg

Use

For treatment of muscle pain, rheumatism and arthritis.

Dosage Suggestion

Adults 3ml maximum per day

Apply on skin and gentle massage around affected areas.

INACTIVE INGREDIENT

Other Ingredients

Cassia, Zanthoxylum piperitum, Rosemary, Peppermint, Lemon, Sesame Oil, Arnica Oil, Walnut Oil.

Directions

Apply on skin and gentle massage around affected area.

Warnings

For external use only. Stop use and ask doctor if rash occurs. Keep out reach of children.

Other Information

Protect this product from excessive heat

and direct sun.

Warnings

For external use only. Stop use and ask doctor if rash occurs. Keep out reach of children.